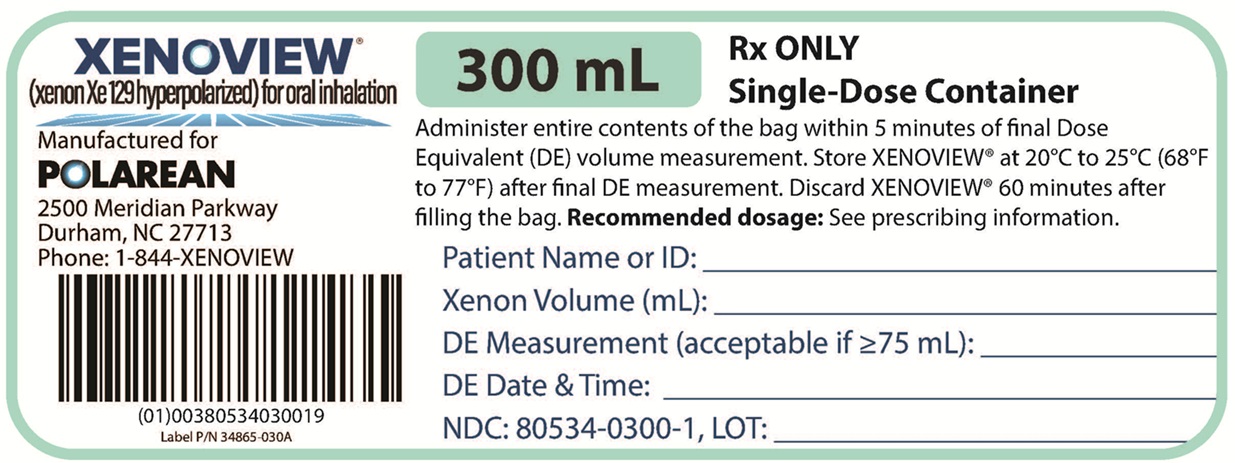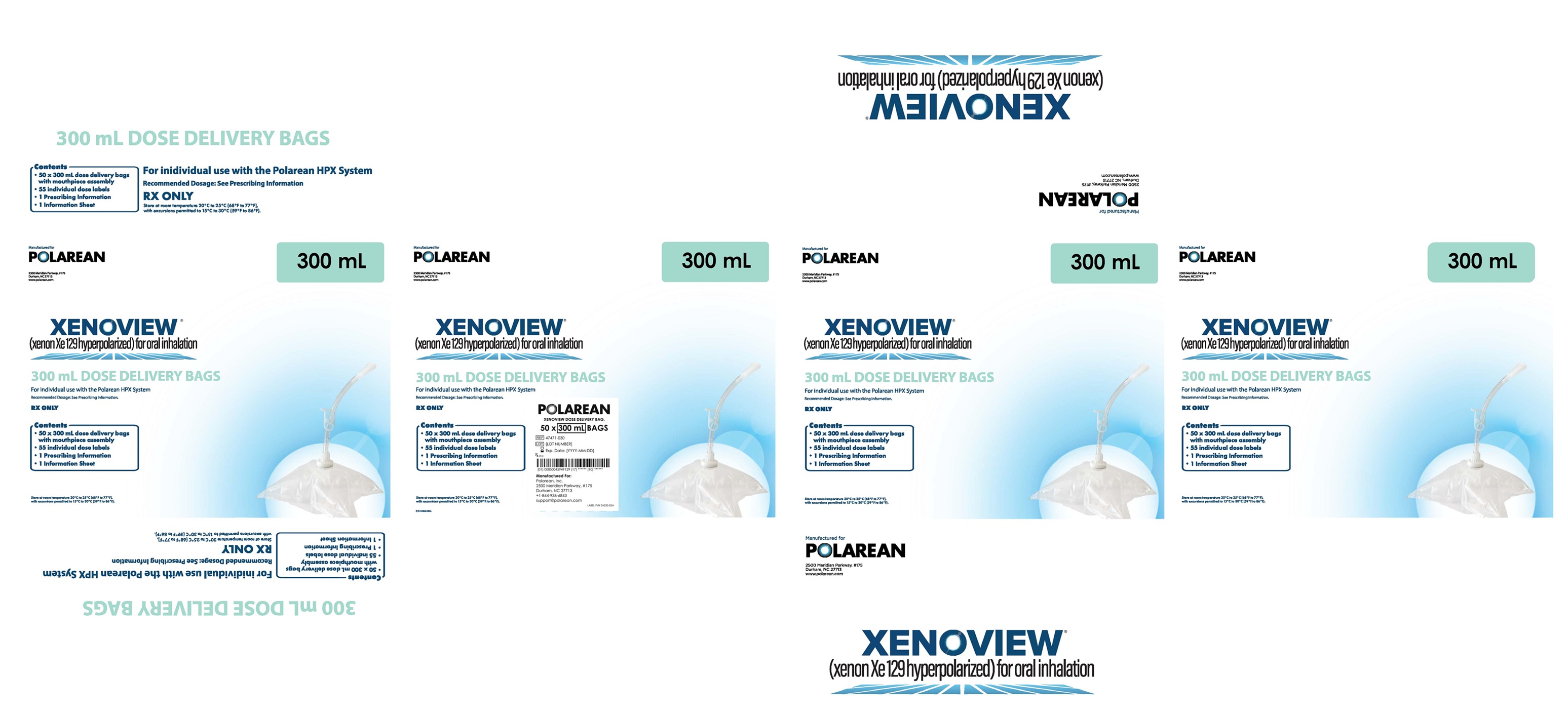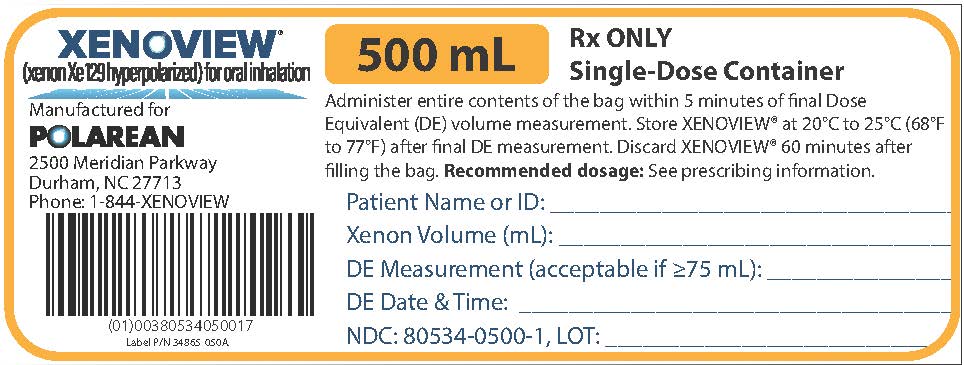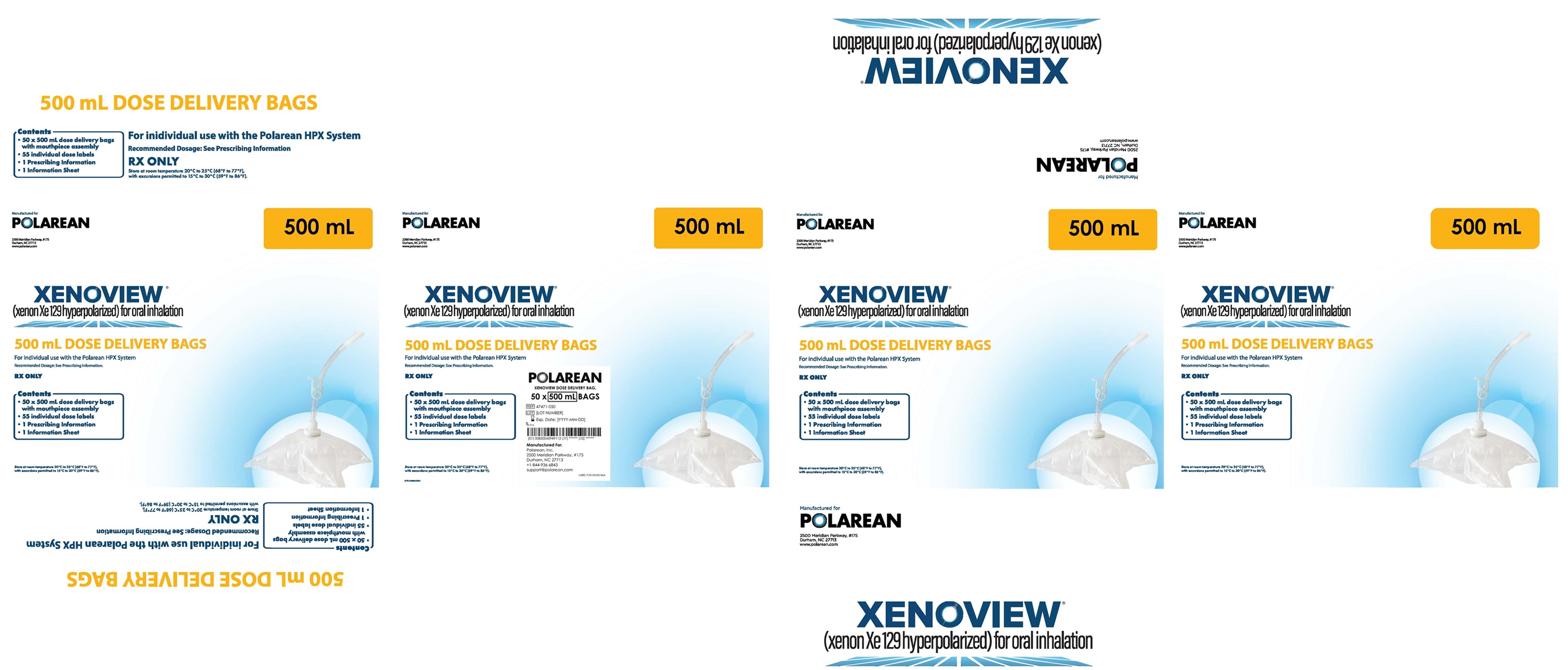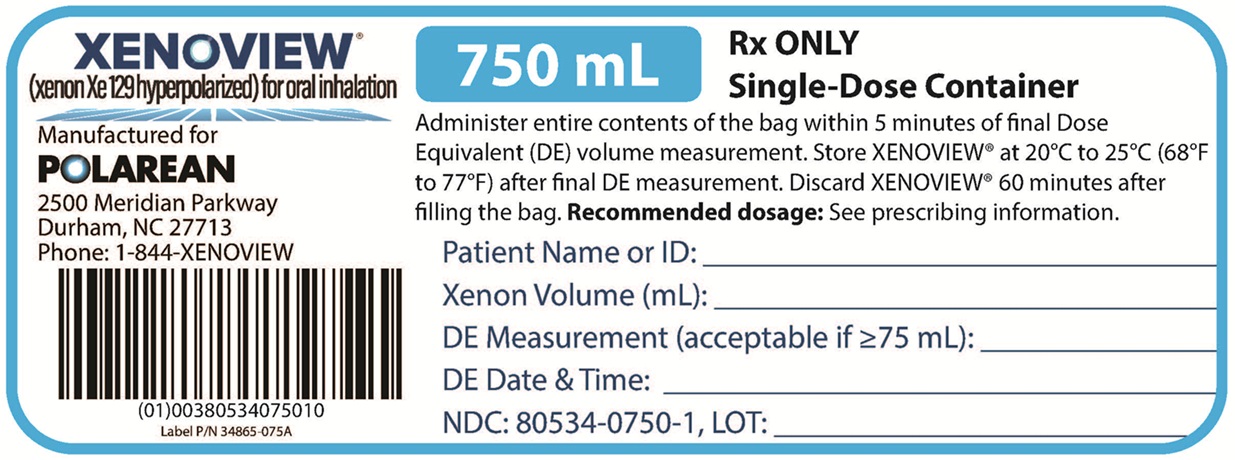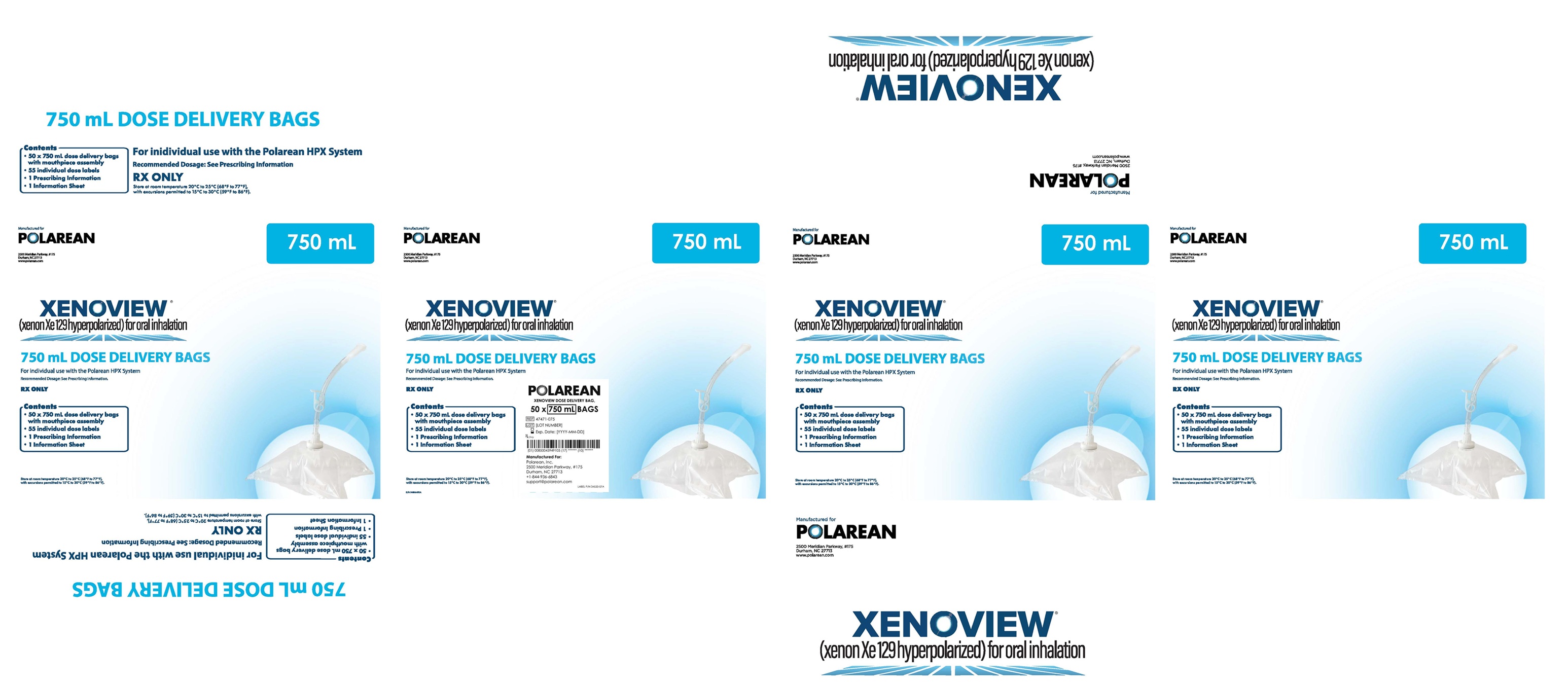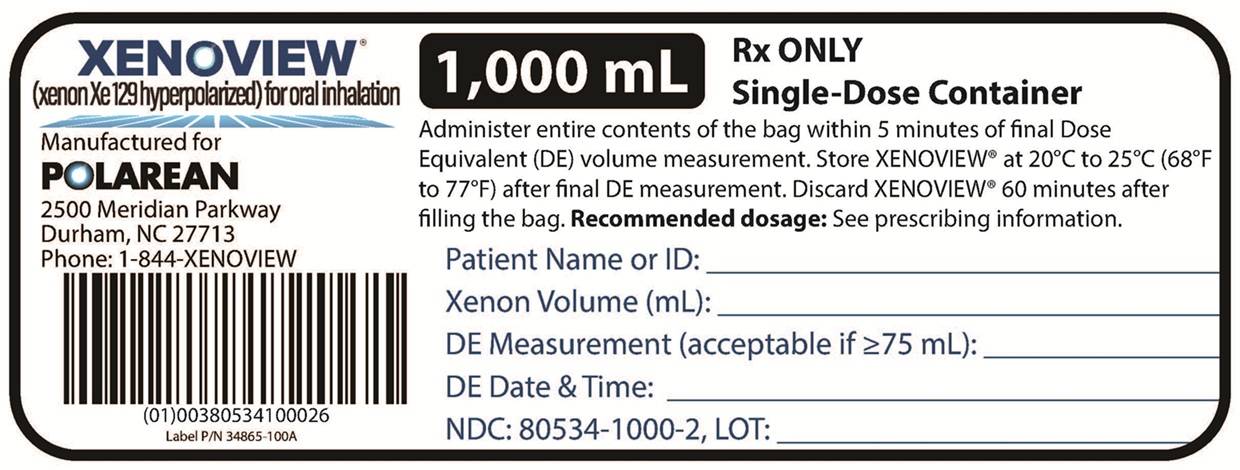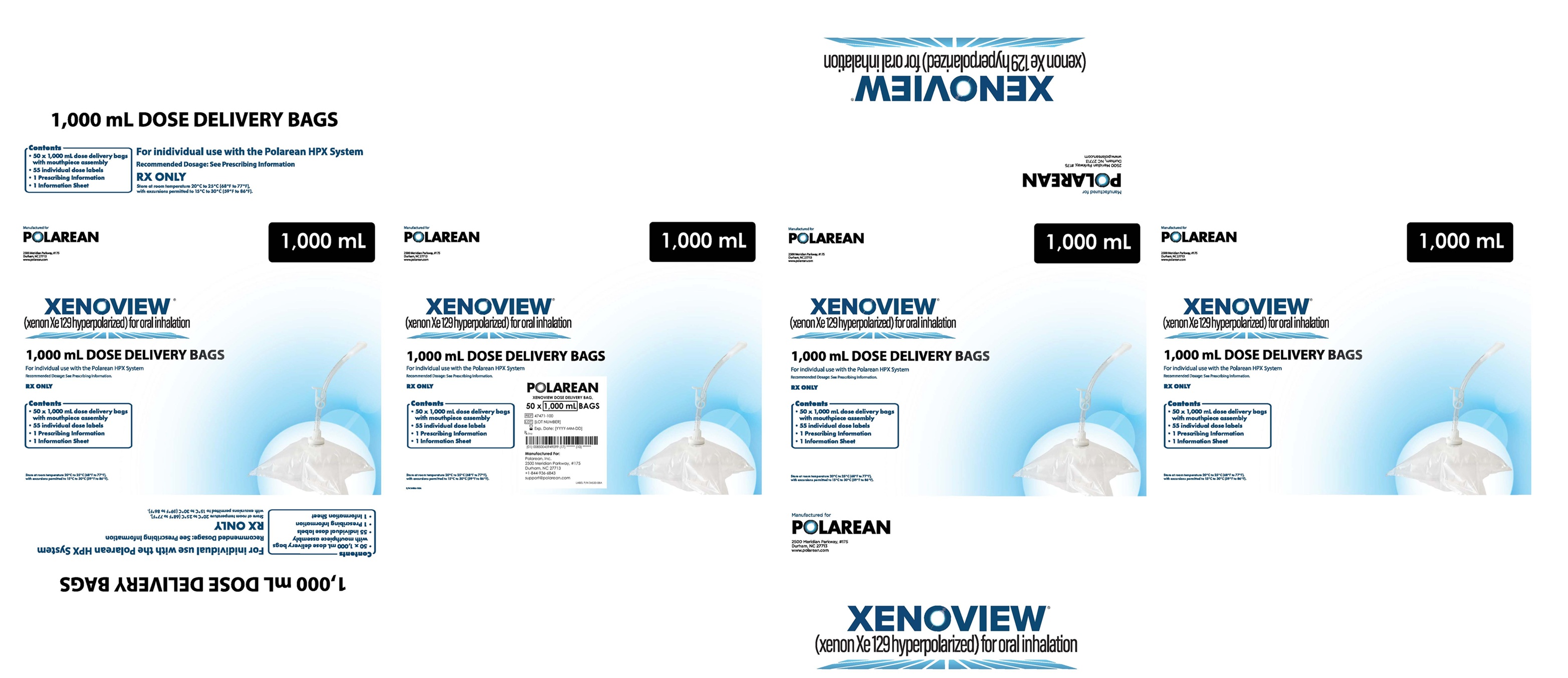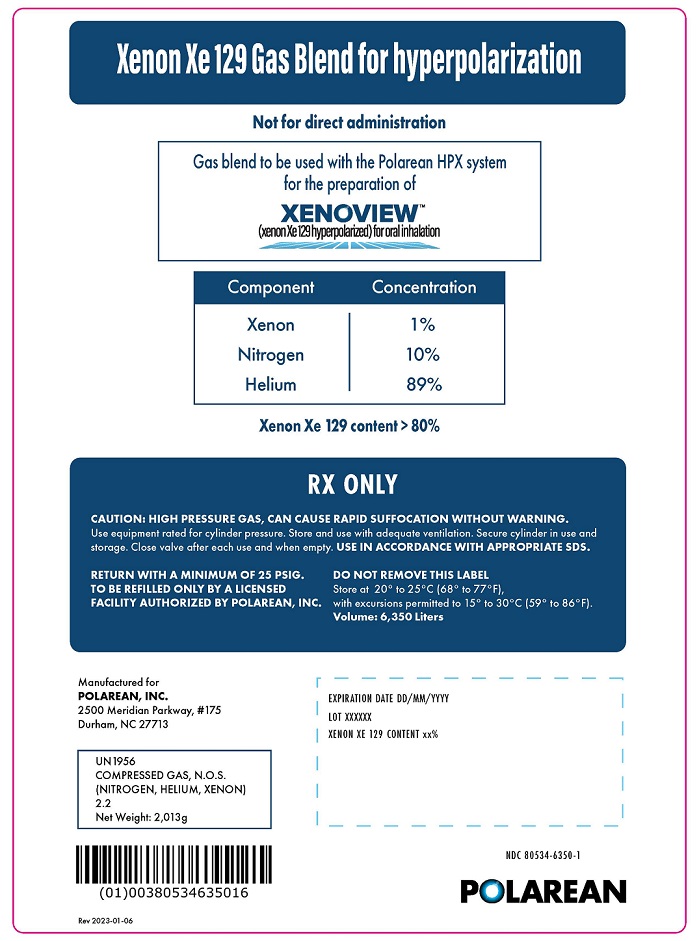 DRUG LABEL: XENOVIEW
NDC: 80534-0300 | Form: GAS
Manufacturer: Polarean, Inc.
Category: prescription | Type: HUMAN PRESCRIPTION DRUG LABEL
Date: 20250530

ACTIVE INGREDIENTS: XENON XE-129, HYPERPOLARIZED 75 mL/300 mL

HIGHLIGHTS OF PRESCRIBING INFORMATION

These highlights do not include all the information needed to use XENOVIEW® safely and effectively. See full prescribing information for XENOVIEW.
XENOVIEW (xenon Xe 129 hyperpolarized), for oral inhalation
Initial U.S. Approval: 2022

RECENT MAJOR CHANGES

Indications and Usage (1) 5/2025

Dosage and Administration 5/2025

Recommended Dosage (2.1)

Preparation, Administration, and Image Acquisition (2.2)

1 INDICATIONS AND USAGE

XENOVIEW, prepared from the Xenon Xe 129 Gas Blend, is a hyperpolarized contrast agent indicated for use with magnetic resonance imaging (MRI) for evaluation of lung ventilation in adults and pediatric patients aged 6 years and older.

Limitations of Use

XENOVIEW has not been evaluated for use with lung perfusion imaging. (1)

2 DOSAGE AND ADMINISTRATION

- The recommended target dose of XENOVIEW for adult and pediatric patients aged 6 years and older is 75 mL to 100 mL Dose Equivalent (DE) volume of hyperpolarized xenon Xe 129 by oral inhalation of the entire contents of one XENOVIEW Dose Delivery Bag. (2.1)
- Choose an appropriate size of the Dose Delivery Bag based on patient’s Total Lung Capacity (TLC) or Forced Vital Capacity (FVC). (2.1)
- Administer dose within 5 minutes of DE measurement. (2.2)
- Initiate imaging immediately after inhalation. (2.2)
- See Full Prescribing Information for detailed information regarding preparation, administration, image acquisition, and image interpretation. (2.2, 2.3)

3 DOSAGE FORMS AND STRENGTHS

- XENOVIEW is a clear, colorless, odorless gas contained in a XENOVIEW Dose Delivery Bag. The bag contains at least 75 mL DE of hyperpolarized xenon Xe 129 in a volume of 250 mL to 750 mL total xenon. The bag total volume administered is 300 mL, 500 mL, 750 mL, or 1,000 mL.
- The dosage strength is DE per volume administered. The minimum DE for a dose of XENOVIEW is 75 mL with a recommended DE target range of 75 mL to 100 mL. DE of greater than 100 mL is acceptable. (3)

4 CONTRAINDICATIONS

None. (4)

5 WARNINGS AND PRECAUTIONS

- Risk of Decreased Image Quality from Supplemental Oxygen: Supplemental oxygen administered simultaneously with XENOVIEW inhalation can cause degradation of image quality. For patients on supplemental oxygen, withhold oxygen inhalation for two breaths prior to XENOVIEW inhalation, and resume oxygen inhalation immediately following the imaging breath hold. (5.1)
- Risk of Transient Hypoxia: Inhalation of an anoxic gas such as XENOVIEW may cause transient hypoxemia in susceptible patients. Monitor all patients for oxygen saturation and symptoms of hypoxemia, and treat as clinically indicated. (5.2)

6 ADVERSE REACTIONS

The adverse reactions (> one patient) in efficacy trials in adults were oropharyngeal pain, headache, and dizziness. (6.1)

To report SUSPECTED ADVERSE REACTIONS, contact Polarean, Inc. at 1‑844-936-6843 or FDA at 1-800-FDA-1088 or www.fda.gov/medwatch.

FULL PRESCRIBING INFORMATION

RECENT MAJOR CHANGES

Indications and Usage (1) 5/2025

Dosage and Administration 5/2025

Recommended Dosage (2.1)

Preparation, Administration, and Image Acquisition (2.2)

1 INDICATIONS AND USAGE

XENOVIEW®, prepared from the Xenon Xe 129 Gas Blend, is indicated for use with magnetic resonance imaging (MRI) for evaluation of lung ventilation in adults and pediatric patients aged 6 years and older.

Limitations of Use

XENOVIEW has not been evaluated for use with lung perfusion imaging.

2 DOSAGE AND ADMINISTRATION

2.1 Recommended Dosage

The recommended target dose of XENOVIEW for adults and pediatric patients aged 6 years and older is 75 mL to 100 mL Dose Equivalent (DE) volume of hyperpolarized xenon Xe 129 by oral inhalation of the entire contents of one XENOVIEW Dose Delivery Bag.

Each bag contains at least 75 mL DE of hyperpolarized xenon Xe 129 measured within 5 minutes of administration, in a volume of 250 mL to 750 mL total xenon with additional nitrogen, NF (99.999% purity) added to reach a total volume of the Dose Delivery Bag.

Select the Dose Delivery Bag based on the patient’s Total Lung Capacity (TLC) according to Table 1. If TLC is not available at the time of the procedure, select the Dose Delivery Bag based on patient’s Forced Vital Capacity (FVC). If neither TLC nor FVC values are available in the patient’s medical records, select the Dose Delivery Bag based on estimates of the patient’s TLC using American Thoracic Society (ATS)-endorsed plethysmography-based predictive equations based on sex and height.

Table 1. Recommended Dose Delivery Bag Volume Based on TLC
TLC (L) | FVC†(L) | Dose Delivery Bag (mL)
<2.0 | <1.5 | 300
2.0 to <3.3 | 1.5 to <2.5 | 500
3.3 to <5.0 | 2.5 to <3.8 | 750
≥5.0 | ≥3.8 | 1,000
†FVC is used when TLC is not available.

The minimum DE for a dose of XENOVIEW is 75 mL with a recommended DE target range of 75 mL to 100 mL. DE of greater than 100 mL is acceptable.

DE is the volume (mL) of 100% isotopically enriched, 100% hyperpolarized, xenon Xe 129 that would produce the equivalent net magnetization as the Xe 129 dose. The HPX Polarization Measurement Station measures DE. DE is defined by the following formula:

DE = (total volume xenon gas) × (fraction of xenon Xe 129 isotopic enrichment in the xenon gas) × (fraction of hyperpolarization)

where the total volume of xenon gas is 250 mL to 750 mL, the fraction of xenon Xe 129 isotopic enrichment is > 80% and the mean fraction of hyperpolarization is no less than 38% to 54% at the completion of polarization of 250 mL of xenon gas.

For example, if 300 mL of total xenon gas with 83% enrichment of xenon Xe 129 is dispensed from the HPX Hyperpolarizer at 40% hyperpolarization:

DE = 300 mL × 0.83 × 0.40 = 99.6 mL

2.2 Preparation, Administration, and Image Acquisition

Preparation

- Choose an appropriate Dose Delivery Bag according to Table 1 [see Dosage and Administration (2.1)].
- Prepare hyperpolarized xenon Xe 129 in the HPX Hyperpolarizer from the Xenon Xe 129 Gas Blend and add Nitrogen, NF (99.999% purity) as necessary to fill the remaining volume in the XENOVIEW Dose Delivery Bag, according to the HPX Hyperpolarization System Operator’s Manual.
- Measure the volume and DE in the XENOVIEW Dose Delivery Bag using the HPX Polarization Measurement Station no more than 5 minutes prior to administration. The DE measurement should be at least 75 mL. Do not use and discard the dose of XENOVIEW® if the volume is determined to be outside of the acceptable range or the DE is less than 75 mL.
- Administer dose within 5 minutes of DE measurement.
- Do not use and discard the dose of XENOVIEW 60 minutes after filling of Dose Delivery Bag.

Administration

- Administer XENOVIEW according to the directions provided in the HPX Hyperpolarization System Operator’s Manual, Administering XENOVIEW.
- Fit the patient with an FDA-cleared Xe 129 chest coil in accordance with the chest coil manufacturer’s instructions for use. The chest coil and MRI scanner must be connected and compatible with one another.
- Position the patient supine with arms either by their side or above their head. Perform conventional ^1H localizer scan, position the desired Xe 129 slices, and prepare the Xe 129 scan.
- For patients on supplemental oxygen, withhold oxygen inhalation for two breaths prior to XENOVIEW inhalation, and resume oxygen inhalation immediately following the imaging breath hold.
- Attach the mouthpiece to the XENOVIEW Dose Delivery Bag.
- With the patient positioned in the MRI scanner, place the mouthpiece in the patient’s mouth and instruct the patient to completely inhale the contents of the XENOVIEW Dose Delivery Bag with a single inhalation.
- Instruct the patient to hold the inhaled breath (up to 15 seconds) during MR image acquisition.

Image Acquisition

- Once the patient has inhaled the full dose of XENOVIEW, begin MRI scanning immediately.
- Upon scan completion, instruct the patient to breathe normally.
- If the image quality is insufficient or if the patient was not able to sufficiently inhale the contents of the XENOVIEW Dose Delivery Bag, the scan can be repeated with a new dose of XENOVIEW.

2.3 Image Display and Interpretation

Evaluation of lung ventilation is based on distribution of XENOVIEW in the lungs.

3 DOSAGE FORMS AND STRENGTHS

XENOVIEW, prepared from the Xenon Xe 129 Gas Blend by the HPX Hyperpolarizer, is a clear, colorless, odorless gas contained in a 300 mL, 500 mL, 750 mL or 1,000 mL XENOVIEW Dose Delivery Bag. Each bag contains at least 75 mL Dose Equivalent (DE) of hyperpolarized xenon Xe 129 in a volume of 250 mL to 750 mL total xenon and a total volume administered of 300 mL, 500 mL, 750 mL, or 1,000 mL.

The strength is DE per volume administered (see Table 2). The minimum DE for a dose of XENOVIEW® is 75 mL with a recommended DE target range of 75 mL to 100 mL. DE of greater than 100 mL is acceptable.

Table 2. Minimum Dosage Strength for Each Dose Delivery Bag
Dose Delivery Bag (mL) | Minimum Dose Equivalent (mL) | Total Volume Administered (mL) | Minimum Dosage Strength*
300 | 75 | 300 | 75 mL DE per 300 mL total volume
500 | 75 | 500 | 75 mL DE per 500 mL total volume
750 | 75 | 750 | 75 mL DE per 750 mL total volume
1,000 | 75 | 1,000 | 75 mL DE per 1,000 mL total volume
*Minimum Dosage Strength = mL Minimum Dose Equivalent per mL Total Volume Administered

4 CONTRAINDICATIONS

None.

5 WARNINGS AND PRECAUTIONS

5.1 Risk of Decreased Image Quality from Supplemental Oxygen

Supplemental oxygen administered simultaneously with XENOVIEW inhalation can cause degradation of image quality due to depolarization of XENOVIEW. For patients on supplemental oxygen, withhold oxygen inhalation for two breaths prior to XENOVIEW inhalation, and resume oxygen inhalation immediately following the imaging breath hold [see Dosage and Administration (2.2)].

5.2 Risk of Transient Hypoxia

Inhalation of an anoxic gas such as XENOVIEW may cause transient hypoxemia in susceptible patients [see Adverse Reactions (6.1)]. Monitor all patients for oxygen desaturation and symptoms of hypoxemia, and treat as clinically indicated.

6 ADVERSE REACTIONS

6.1 Clinical Trials Experience

Because clinical trials are conducted under widely varying conditions, adverse reaction rates observed in the clinical trials of a drug cannot be directly compared to rates in the clinical trials of another drug and may not reflect the rates observed in practice.

Adverse Reactions in Adult Patients

The safety of XENOVIEW was evaluated in two prospective efficacy trials that enrolled a total of 83 adult patients with various lung disorders who were being evaluated for possible lung surgery [see Clinical Studies (14)]. Mean age of these patients was 62 years, 88% were White and 69% were male. In these two trials, mean xenon gas volume per XENOVIEW dose was 330.2 mL and 81 of 83 patients (98%) received a single administration of XENOVIEW. For safety assessment, the volume of administered xenon gas in the XENOVIEW dose is noted rather than the DE, because isotopic enrichment and hyperpolarization are not known to affect the safety profile of xenon gas.

Adverse reactions were reported in 12 (14%) of the 83 patients. Adverse reactions reported by more than one patient were oropharyngeal pain (n = 4 patients), headache (n = 2 patients), and dizziness (n = 2 patients).

A hypersensitivity reaction that included transient pruritus and erythema occurred in one patient with a history of allergic reactions to several drugs, foods, and other substances.

In pooled data of 123 adult patients from published studies, most of whom had lung disorders such as COPD, idiopathic pulmonary fibrosis, and asthma, who received 1 dose to 2 doses of hyperpolarized xenon Xe 129 with xenon volumes of approximately 500 mL to 1,000 mL of xenon gas per dose, the following transient adverse reactions were reported: numbness, tingling, euphoria, and dizziness. Overall frequency of these adverse reactions could not be determined from the published information.

Adverse Reactions in Pediatric Patients

In pooled data of 120 pediatric patients aged 6 to 18 years from published studies, most of whom had either asthma or cystic fibrosis, who received 1 dose to 2 doses of hyperpolarized xenon Xe 129 with xenon volumes based on predicted TLC, the following transient adverse reactions were reported: blood oxygen desaturation, heart rate elevation, numbness, tingling, dizziness, and euphoria. Overall frequency of these adverse reactions could not be determined from the published information.

In one of the published studies of 23 pediatric patients aged 6 to 18 years, 11 of whom had cystic fibrosis and 12 of whom were healthy, the mean difference of SpO2% from baseline was -6% following hyperpolarized xenon Xe 129 administration with xenon volumes based on predicted total lung capacity. In the same study, the mean change in heart rate from baseline was +6.6 beats per minute following hyperpolarized xenon Xe 129 administration. Both reported oxygen desaturation and heart rate elevation resolved by 2 minutes post-dose without intervention.

8 USE IN SPECIFIC POPULATIONS

8.1 Pregnancy

Risk Summary

XENOVIEW is minimally absorbed systemically following the inhalation route of administration, and maternal use is not expected to result in fetal exposure to the drug [see Clinical Pharmacology (12.3)]. Adequately designed animal reproduction studies have not been conducted with hyperpolarized xenon Xe 129. Although not adequately designed to evaluate reproductive and developmental toxicity, there are animal reproduction data available in the literature. Animal reproduction studies were conducted in rats by administering an 80% Xe/20% O2 gas mixture for 2 hours twice a week for 2 and 10 weeks, with no observed effects on fertility or pregnancy. Gas mixtures containing 70% to 75% Xe gas and 25% to 30% O2 gas were found to be non-teratogenic in rats when administered for 24 hours. In a separate study, rats were administered an 80%/20% Xe/O2 gas mixture for 2 hours twice a week from the first to nineteenth day of pregnancy with no observed effects on embryo-fetal development or signs of teratogenicity.

The background risk of major birth defects and miscarriage for the indicated population is unknown. All pregnancies have a background risk of birth defect, loss, or other adverse outcomes. In the U.S general population, the estimated background risks of major birth defects and miscarriage in clinically recognized pregnancies are 2% to 4% and 15% to 20%, respectively.

8.2 Lactation

Risk Summary

XENOVIEW® is minimally absorbed systemically following the inhalation route of administration, and breastfeeding is not expected to result in exposure of the infant to the drug [see Clinical Pharmacology (12.3)]. There is no information on the presence of hyperpolarized xenon Xe 129 in human milk, the effect on the breastfed infant, or the effect on milk production. The developmental and health benefits of breastfeeding should be considered along with the mother’s clinical need for XENOVIEW® and any potential adverse effects on the breastfed child from XENOVIEW or from the underlying maternal condition.

8.4 Pediatric Use

The safety and effectiveness of XENOVIEW have been established in pediatric patients aged 6 years and older for use with MRI to evaluate lung ventilation. Use of XENOVIEW in this age group is supported by evidence from adequate and well-controlled studies in adults with additional safety data from published studies [see Adverse Reactions (6.1) and Clinical Studies (14)].

Safety and effectiveness of XENOVIEW have not been established in pediatric patients less than 6 years of age.

8.5 Geriatric Use

Of the total number of patients in clinical studies of XENOVIEW, 36 (43%) were 65 years of age and older, while 6 (7%) were 75 years of age and older. No overall differences in safety or effectiveness have been observed between patients 65 years of age and older and younger adult patients although the number of patients in the trials was not large enough to allow definitive comparison.

11 DESCRIPTION

XENOVIEW (xenon Xe 129 hyperpolarized) is a hyperpolarized contrast agent produced on site by the HPX Hyperpolarization System from the isotopically enriched Xenon Xe 129 Gas Blend. The Gas Blend cylinder distributed by Polarean contains xenon (1% total; > 80% isotopic purity Xe 129), nitrogen, NF (10%), and helium, NF (89%).

The active pharmaceutical ingredient in XENOVIEW is hyperpolarized xenon Xe 129. Hyperpolarized xenon Xe 129 is chemically identical to non-polarized xenon Xe 129. Xenon is a clear, colorless, monoatomic, inert, stable, noble gas. It is naturally abundant in air at a level of 0.087 ppm. Atmospheric xenon is composed of nine non-radioactive isotopes, of which xenon Xe 129 comprises 26.4%. The atomic weight of xenon Xe 129 is 128.9.

XENOVIEW is a clear, colorless, odorless gas for oral inhalation use. Each XENOVIEW Dose Delivery Bag contains a Dose Equivalent (DE) volume of hyperpolarized xenon Xe 129 in a volume of 250 mL to 750 mL total xenon with additional nitrogen, NF (99.999% purity) added as an inert buffer to ensure the total volume of gas reaches the dose delivery bag volume (300 mL, 500 mL, 750 mL, or 1,000 mL). The minimum DE for a dose of XENOVIEW is 75 mL with a recommended DE target range of 75 to 100 mL. DE of greater than 100 mL is acceptable.

12 CLINICAL PHARMACOLOGY

12.1 Mechanism of Action

When hyperpolarized xenon Xe 129 gas is inhaled, a multi-nuclear capable MRI scanner can be used to image the hyperpolarized xenon Xe 129 distribution throughout the ventilated lung. Hyperpolarized xenon Xe 129 nuclei are directly detected by a Xe 129 MRI coil.

12.2 Pharmacodynamics

The MRI signal of hyperpolarized xenon Xe 129 is dependent on the volume of the xenon gas inhaled, degree of xenon Xe 129 isotopic enrichment, and degree of hyperpolarization [see Dosage and Administration (2.1)].

12.3 Pharmacokinetics

The pharmacokinetics of hyperpolarized xenon Xe 129 are similar to those of non-polarized xenon.

Distribution

Xenon is a readily diffusible gas. Inhalation of xenon results in dispersion in the ventilated areas of the lung with uptake of a small amount of xenon into the pulmonary vessels followed by distribution to more distal organs. The solubility of xenon is higher in fatty tissues than in aqueous tissues and body compartments such as plasma.

Elimination

Following a single breath hold, xenon is eliminated through exhalation with an elimination half-life of 14.5 seconds for a 75% Xe/25% N2 gas mixture and 14.3 seconds for a 25% Xe/75% N2 gas mixture.

13 NONCLINICAL TOXICOLOGY

13.1 Carcinogenesis, Mutagenesis, Impairment of Fertility

No studies evaluating mutagenic or carcinogenic potential have been performed.

14 CLINICAL STUDIES

The safety and efficacy of XENOVIEW® were evaluated in two prospective, multi-center, randomized, open-label, cross-over clinical trials that compared XENOVIEW MRI to xenon Xe 133 scintigraphy in adult patients with pulmonary disorders: Study 1 (NCT03417687) and Study 2 (NCT03418090). The mean XENOVIEW dose used in these trials was 99 mL DE of hyperpolarized xenon Xe 129 at the time of measurement within 5 minutes of administration.

Study 1

Study 1 compared XENOVIEW and xenon Xe 133 imaging in patients being evaluated for possible lung resection surgery with respiratory disorders including: pulmonary mass (44%), COPD (35%), cough (15%), sleep apnea syndrome (12%), and asthma (12%). A total of 32 patients, with a mean age of 62 years (range 25 to 77 years) of whom 78% were White and 69% were male, completed both scans.

On each XENOVIEW and xenon Xe 133 scan, the fraction of total signal in the lungs was calculated in each of six zones consisting of upper, middle, and lower regions in each lung. These values were used to estimate the post-operative percentage of lung ventilation predicted to remain after planned resection of a pre-specified lung area.

One of the 32 patients who completed both scans was excluded from the primary analysis because no planned resection area was recorded. In the remaining 31 patients, the mean within-patient difference in the predicted post-operative percentage of remaining lung ventilation between XENOVIEW and xenon Xe 133 imaging was within a pre-specified equivalence interval with an observed estimate of 1.4% (95% confidence interval: -0.8%, 3.6%). In an exploratory analysis that standardized the within-patient difference of the predicted remaining lung ventilation between XENOVIEW and xenon Xe 133 imaging to each patient’s xenon Xe 133 results, the percentage of patients who had standardized differences within ± 10%, ± 15%, and ± 20% were 81% (25/31), 94% (29/31), and 94% (29/31), respectively.

Study 2

Study 2 compared XENOVIEW and xenon Xe 133 imaging in patients being evaluated for possible lung transplant surgery with respiratory disorders including: interstitial lung disease (49%), idiopathic pulmonary fibrosis (29%), COPD (22%), sleep apnea syndrome (16%), other pulmonary fibrosis (14%), allergic rhinitis (12%), and cough (10%). A total of 49 patients, with a mean age of 62 years (range 19 to 77 years), of whom 94% were White and 69% were male, completed both scans.

On each XENOVIEW® and xenon Xe 133 scan, right lung signal and total signal in the lungs were calculated and used to estimate the percentage of overall lung ventilation contributed by the right lung.

In the primary analysis of the 49 patients who completed both scans, the mean within-patient difference in the percentage of overall lung ventilation contributed by the right lung between XENOVIEW and xenon Xe 133 imaging was within a pre-specified equivalence interval with an observed estimate of 1.6% (95% confidence interval: -3.7%, 0.5%). In an exploratory analysis that standardized the within-patient difference of right lung ventilation between XENOVIEW and xenon Xe 133 imaging to that of each patient’s xenon Xe 133 results, the percentage of patients who had standardized differences of ± 10%, ± 15%, and ± 20% were 65% (32/49), 80% (39/49), and 96% (47/49), respectively.

16 HOW SUPPLIED

How Supplied

XENOVIEW (xenon Xe 129 hyperpolarized) is prepared from the Xenon Xe 129 Gas Blend by the HPX Hyperpolarizer and is contained in a XENOVIEW Dose Delivery Bag as a clear, colorless, odorless gas.

XENOVIEW Dose Delivery Bags are available in four different sizes co-packaged with attachable mouthpieces and affixable dose labels:

- 300 mL bags in a box of 50 (NDC 80534-0300-1)
- 500 mL bags in a box of 50 (NDC 80534-0500-1)
- 750 mL bags in a box of 50 (NDC 80534-0750-1)
- 1,000 mL bags in a box of 50 (NDC 80534-1000-2)

Xenon Xe 129 Gas Blend for preparation of XENOVIEW is supplied as a compressed gas under high pressure (2,105 pounds per square inch gauge [psig]) in size 302 aluminum cylinders with a volume of 6,350 liters (NDC 80534-6350-1).

Storage and Handling

Store XENOVIEW at 20° to 25°C (68° to 77°F) for no more than 5 minutes after final DE measurement. Do not use and discard XENOVIEW 60 minutes after filling of Dose Delivery Bag.

Store Xenon Xe 129 Gas Blend at 20° to 25°C (68° to 77°F), with excursions permitted to 15°C to 30°C (59°F to 86°F).

Manufactured for:

Polarean, Inc.

2500 Meridian Parkway, #175

Durham, NC 27713

Tel: +1-844-936-6843

XENOVIEW® is a trademark of Polarean, Inc.

Doc #: 34660D

PRINCIPAL DISPLAY PANEL - NDC 80534-0300-1

XENOVIEW Dose Delivery Bag (300 mL)

NDC 80534-0300-1

XENOVIEW Carton of Delivery Bags (50 bags with attachable mouthpieces and affixable dose labels)

PRINCIPAL DISPLAY PANEL - NDC 80534-0500-1

XENOVIEW Dose Delivery Bag (500 mL)

NDC 80534-0500-1

XENOVIEW Carton of Delivery Bags (50 bags with attachable mouthpieces and affixable dose labels)

PRINCIPAL DISPLAY PANEL - NDC 80534-0750-1

XENOVIEW Dose Delivery Bag (750 mL)

NDC 80534-0750-1

XENOVIEW Carton of Delivery Bags (50 bags with attachable mouthpieces and affixable dose labels)

PRINCIPAL DISPLAY PANEL - NDC 80534-1000-2

XENOVIEW Dose Delivery Bag (1,000 mL)

NDC 80534-1000-2

XENOVIEW Carton of Delivery Bags (50 bags with attachable mouthpieces and affixable dose labels)

PRINCIPAL DISPLAY PANEL - NDC 80534-6350-1

Xenon Xe 129 Gas Blend for Preparation of XENOVIEW Compressed Gas Cylinders

NDC 80534-6350-1